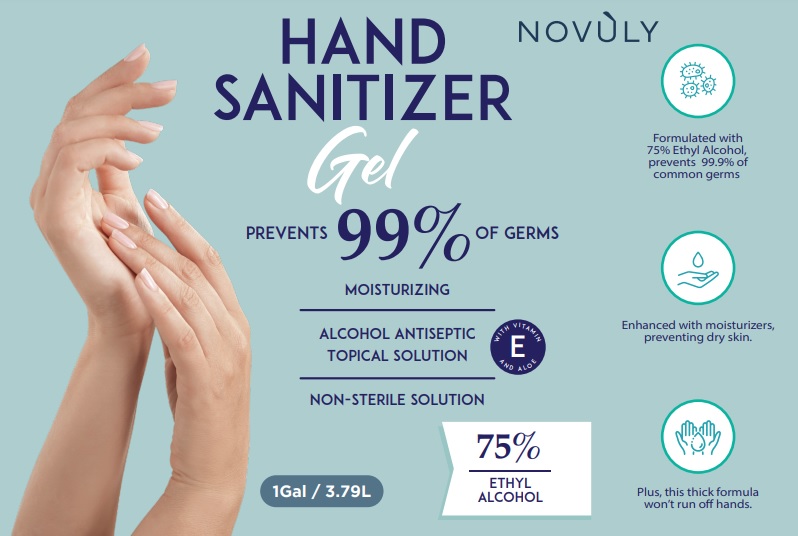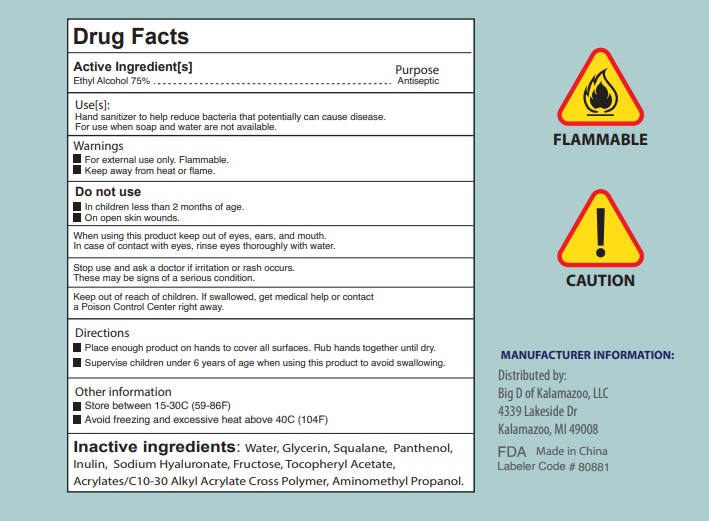 DRUG LABEL: Novuly Hand Sanitizer
NDC: 80881-001 | Form: GEL
Manufacturer: Big D of Kalamazoo, LLC
Category: otc | Type: HUMAN OTC DRUG LABEL
Date: 20210210

ACTIVE INGREDIENTS: ALCOHOL 75 L/100 L
INACTIVE INGREDIENTS: GLYCERIN; PANTHENOL; WATER; FRUCTOSE; ALPHA-TOCOPHEROL ACETATE; AMINOMETHYL PROPANEDIOL; PEG-9 DIGLYCIDYL ETHER/SODIUM HYALURONATE CROSSPOLYMER; CARBOMER COPOLYMER TYPE A; SQUALENE; INULIN

Novuly Hand Sanitizer Gel (1 Gal, 3.79L)

Active Ingredient(s)

Alcohol 75% v/v. Purpose: Antiseptic

Purpose

Antiseptic

Use

Hand sanitizer to help reduce bacteria that potentially can cause disease.
For use when soap and water are not available.

Warnings

For external use only. Flammable. Keep away from heat or flame

Do not use

- in children less than 2 months of age
- on open skin wounds

When using this product keep out of eyes, ears, and mouth. In case of contact with eyes, rinse eyes thoroughly with water.
Stop use and ask a doctor if irritation or rash occurs. These may be signs of a serious condition.
Keep out of reach of children. If swallowed, get medical help or contact a Poison Control Center right away.

Stop use and ask a doctor if irritation or rash occurs. These may be signs of a serious condition.

Keep out of reach of children. If swallowed, get medical help or contact a Poison Control Center right away.

Directions

- Place enough product on hands to cover all surfaces. Rub hands together until dry.
- Supervise children under 6 years of age when using this product to avoid swallowing.

Other information

- Store between 15-30C (59-86F)
- Avoid freezing and excessive heat above 40C (104F)

Inactive ingredients

Water, Glycerin, Squalane, Panthenol, Inulin, Sodium Hyaluronate, Fructose, Tocopheryl Acetate, Acrylates/C10-30 Alkyl Acrylate Cross Polymer, Aminomethyl Propanol

Package Label - Principal Display Panel

1Gal (3.79L) NDC:80881-001-01

Manufacturer Information:

Made In China
Distributed by:
Big D of Kalamazoo, LLC
4339 Lakeside Dr
Kalamazoo, MI 49008
FDA
Labeler Code # 80881